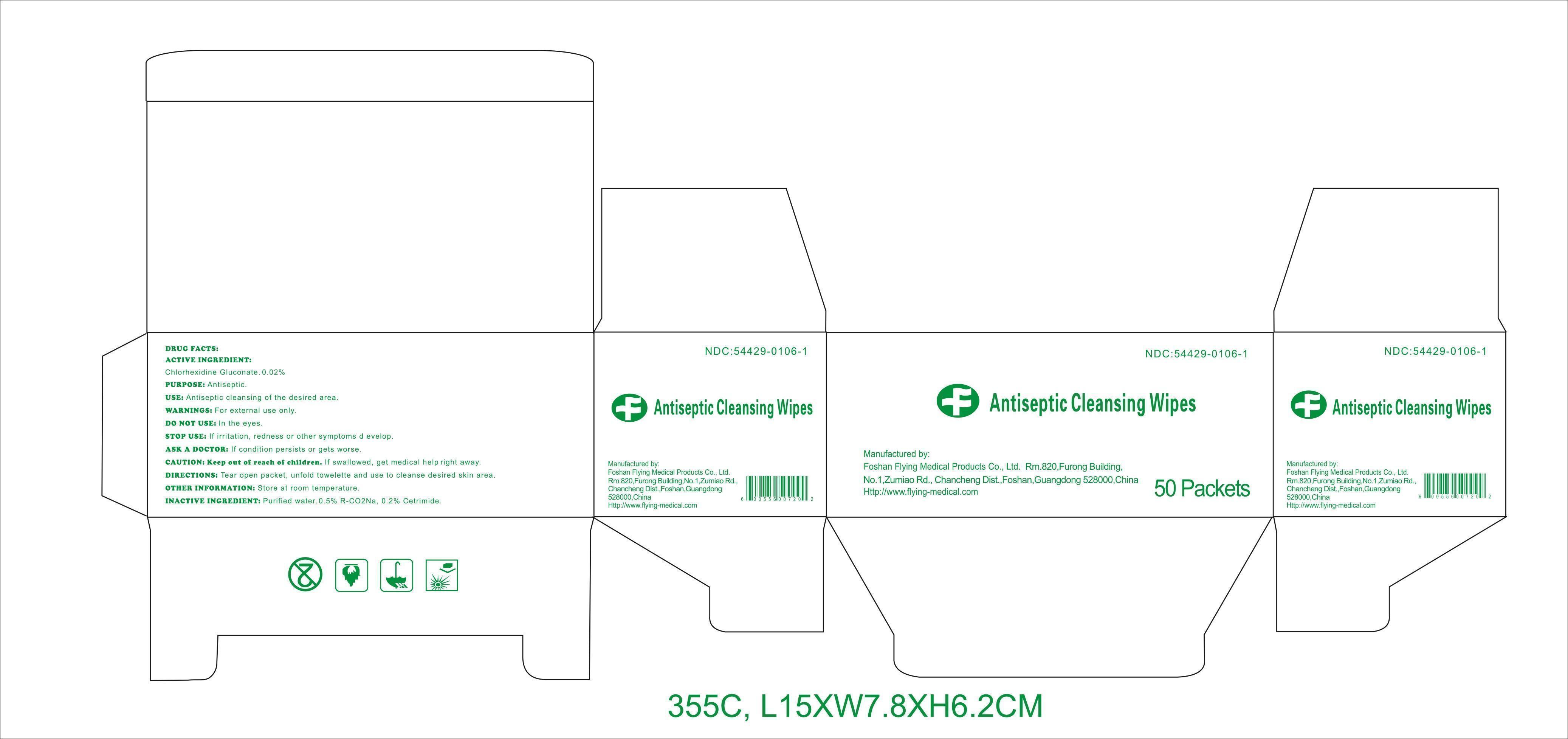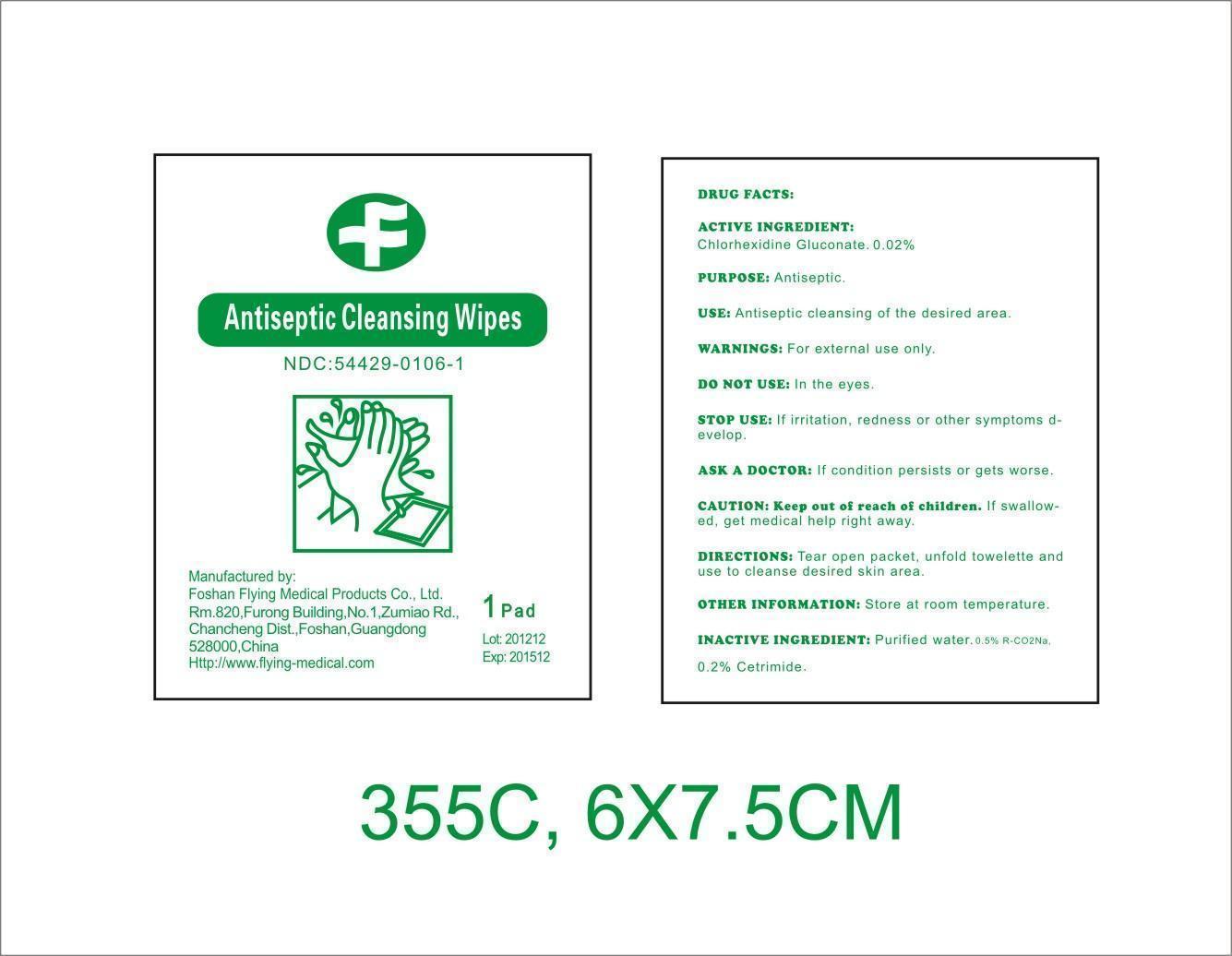 DRUG LABEL: Antiseptic Cleansing Wipes
NDC: 54429-0106 | Form: SWAB
Manufacturer: Foshan Flying Medical Products Co., Ltd.
Category: otc | Type: HUMAN OTC DRUG LABEL
Date: 20181008

ACTIVE INGREDIENTS: CHLORHEXIDINE GLUCONATE 0.0002 mg/1 mg
INACTIVE INGREDIENTS: WATER; CETRIMIDE

Antiseptic Cleansing Wipes

Active ingredient

Chlorhexidine Gluconate 0.02%

Purpose

Antiseptic

CAUTION: Keep out of reach of children

If swallowed, get medical help or contact Poison Control Center right away.

Use

Antiseptic cleansing of the desired area.

Warnings

For external use only. Flammable, keep away from fire or flame.

Do not use

in the eyes.

Stop use

If irritation, redness or other symptoms develop.

Ask a doctor

If condition persists or gets worse.

Directions

Tear open packet, unfold towelette, and use to cleanse desired skin area.

Inactive ingredients

Purified water, 0.5% R-CO2Na, 0.2% Cetrimide

DRUG FACTS

Active ingredient

Chlorhexidine Gluconate 0.02%

Purpose

Antiseptic

Use

Antiseptic cleansing of the desired area.

Warnings

For external use only.

Do notuse

﹒in the eyes.

Stop use

If irritation, redness or other symptoms develop.

Ask a doctor

If condition persists or gets worse.

CAUTION: Keep out of reach of children.

If swallowed, get medical help right away.

Directions

Tear open packet, unfold towelette, and use to cleanse desired skin area.

Other information: Store at room temperature.

Inactive ingredients

Purified water, 0.5% R-CO2Na, 0.2% Cetrimide